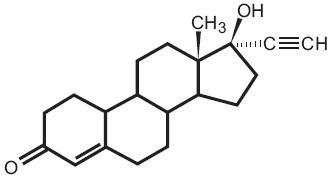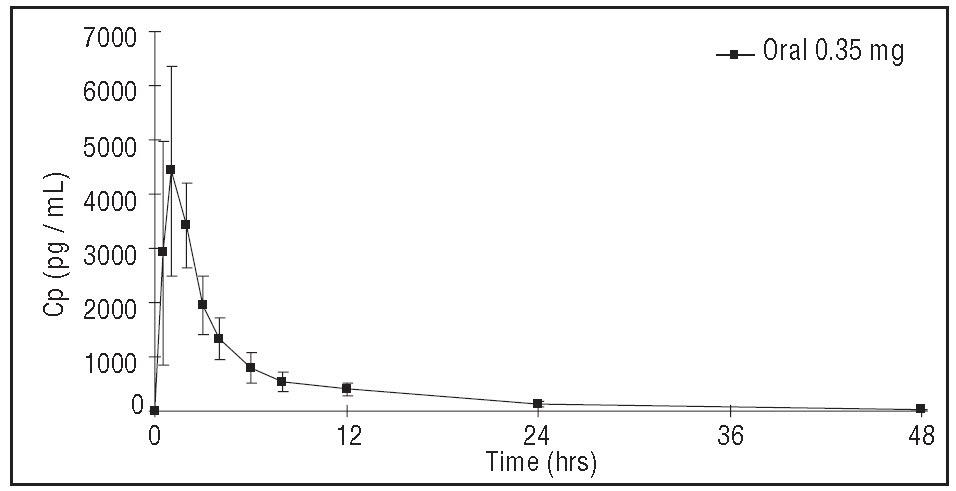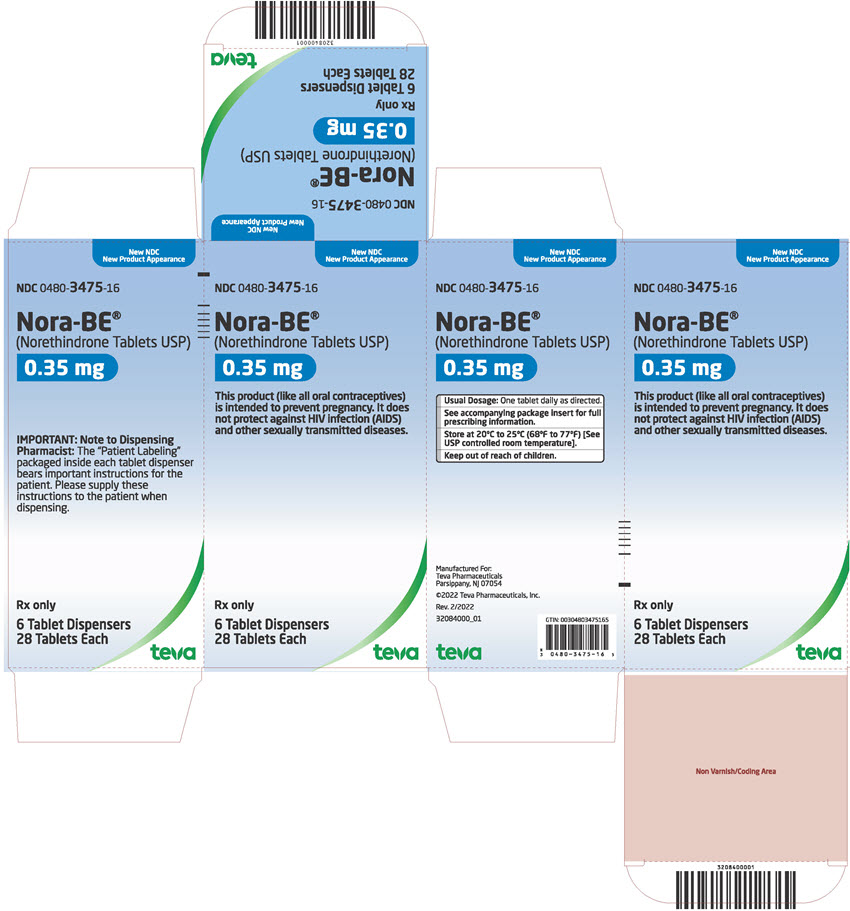 DRUG LABEL: Nora BE
NDC: 0480-3475 | Form: TABLET
Manufacturer: Teva Pharmaceuticals, Inc.
Category: prescription | Type: HUMAN PRESCRIPTION DRUG LABEL
Date: 20240402

ACTIVE INGREDIENTS: NORETHINDRONE 0.35 mg/1 1
INACTIVE INGREDIENTS: LACTOSE, UNSPECIFIED FORM; MAGNESIUM STEARATE; POVIDONE; STARCH, CORN

Nora-BE®
(Norethindrone 0.35 mg tablets USP)

PHYSICIAN LABELING
Patients should be counseled that oral contraceptives do not protect against transmission of HIV (AIDS) and other sexually transmitted diseases (STDs) such as Chlamydia, genital herpes, genital warts, gonorrhea, hepatitis B, and syphilis.

DESCRIPTION

Each white Nora-BE® tablet provides a continuous oral contraceptive regimen of 0.35 mg norethindrone daily, and the inactive ingredients include lactose, magnesium stearate, povidone, and starch.

The chemical name for norethindrone is 17-Hydroxy-19-Nor-17α-pregn-4-en-20-yn-3-one. The structural formula follows:

norethindrone

Therapeutic class = oral contraceptive.

CLINICAL PHARMACOLOGY

1. Mode of Action. Nora-BE progestin-only oral contraceptives prevent conception by suppressing ovulation in approximately half of users, thickening the cervical mucus to inhibit sperm penetration, lowering the mid-cycle LH and FSH peaks, slowing the movement of the ovum through the fallopian tubes, and altering the endometrium.

2. Pharmacokinetics.
Absorption: Norethindrone is rapidly absorbed with maximum plasma concentrations occurring within 1 to 2 hours after Nora-BE administration (see Table 1). Norethindrone appears to be completely absorbed following oral administration; however, it is subject to first pass metabolism resulting in an absolute bioavailability of approximately 65%.

Figure 1: Mean ± SD Norethindrone Plasma Concentrations Following Nora-BE Administration.

Peak plasma concentrations occur approximately 1 hour after administration (mean Tmax 1.2 hours). The mean (SD) Cmax was 4816.8 (1532.6) pg/mL and generally occurred within 1 hour (mean) of tablet administration, ranging from 0.5 to 2 hours. The mean (SD) Cavg was 885 (250) pg/mL, however, the mean concentration at 24 hrs was 130 (47) pg/mL.

Table 1 provides summary statistics of the pharmacokinetic parameters associated with single dose Nora-BE administration.

Table 1: Mean ± SD Pharmacokinetic Parameters Following Single Dose Administration of Nora-BE in 12 Healthy Female Subjects Under Fasting Conditions

Pharmacokinetic Parameter | Norethindrone 0.35 mg
Tmax (hr) | 1.2 ± 0.5
Cmax (pg/mL) | 4817 ± 1533
AUC(0-48) (pg•h/mL) | 21233 ± 6002
t 1/2 (h) | 7.7 ± 0.5

The food effect on the rate and extent of norethindrone absorption after Nora-BE administration has not been evaluated.

Distribution: Following oral administration, norethindrone is 36% bound to sex hormone-binding globulin (SHBG) and 61% bound to albumin. Volume of distribution of norethindrone is approximately 4 L/kg.

Metabolism: Norethindrone undergoes extensive biotransformation, primarily via reduction, followed by sulfate and glucuronide conjugation; less than 5% of a norethindrone dose is excreted unchanged; greater than 50% and 20-40% of a dose is excreted in urine and feces, respectively. The majority of metabolites in the circulation are sulfate, with glucuronides accounting for most of the urinary metabolites.

Excretion: Plasma clearance rate for norethindrone has been estimated to be approximately 600 L/day. Norethindrone is excreted in both urine and feces, primarily as metabolites. The mean terminal elimination half-life of norethindrone following single dose administration of Nora-BE is approximately 8 hours.

INDICATIONS AND USAGE

1. Indications. Progestin-only oral contraceptives are indicated for the prevention of pregnancy.

2. Efficacy. If used perfectly, the first-year failure rate for progestin-only oral contraceptives is 0.5%. However, the typical failure rate is estimated to be closer to 5%, due to late or omitted pills. The following table lists the pregnancy rates for users of all major methods of contraception.

Table 2: Percentage of Women Experiencing an Unintended Pregnancy During the First Year of Typical Use and the First Year of Perfect Use of Contraception and the Percentage Continuing Use at the End of the First Year. United States.
 | % of Women Experiencing an Unintended Pregnancy within the First Year of Use |  | % of Women Continuing Use at One Year^3
Method (1) | Typical Use^1 (2) | Perfect Use^2 (3) | (4)
Chance^4 | 85 | 85
Spermicides^5 | 26 | 6 | 40
Periodic abstinence | 25 |  | 63
Calendar |  | 9
Ovulation Method |  | 3
Sympto-Thermal^6 |  | 2
Post-Ovulation |  | 1
Cap^7
Parous Women | 40 | 26 | 42
Nulliparous Women | 20 | 9 | 56
Sponge
Parous Women | 40 | 20 | 42
Nulliparous Women | 20 | 9 | 56
Diaphragm^7 | 20 | 6 | 56
Withdrawal | 19 | 4
Condom^8
Female (Reality) | 21 | 5 | 56
Male | 14 | 3 | 61
Pill | 5 |  | 71
Progestin only |  | 0.5
Combined |  | 0.1
IUDs
Progesterone T | 2.0 | 1.5 | 81
Copper T380A | 0.8 | 0.6 | 78
LNg 20 | 0.1 | 0.1 | 81
Depo-Provera® | 0.3 | 0.3 | 70
Levonorgestrel Implants (Norplant®) | 0.05 | 0.05 | 88
Female Sterilization | 0.5 | 0.5 | 100
Male Sterilization | 0.15 | 0.10 | 100

Emergency Contraceptive Pills: Treatment initiated within 72 hours after unprotected intercourse reduces the risk of pregnancy by at least 75%.^9

Lactational Amenorrhea Method: LAM is a highly effective, temporary method of contraception.^10

Source: Trussell, J, Contraceptive Efficacy. In: Hatcher RA, Trussell J, Stewart F, Cates W, Stewart GK, Kowal D, Guest F, Contraceptive Technology: Seventeenth Revised Edition. New York NY: Irvington Publishers, 1998.

1. Among typical couples who initiate use of a method (not necessarily for the first time), the percentage who experience an accidental pregnancy during the first year if they do not stop use for any reason.
2. Among couples who initiate use of a method (not necessarily for the first time), and who use it perfectly (both consistently and correctly), the percentage who experience an accidental pregnancy during the first year if they do not stop use for any other reason.
3. Among couples attempting to avoid pregnancy, the percentage who continue to use a method for one year.
4. The percentage of women becoming pregnant noted in columns (2) and (3) are based on data from populations where contraception is not used and from women who cease using contraception in order to become pregnant. Among such populations, about 89% become pregnant within one year. This estimate was lowered slightly (to 85%) to represent the percentage that would become pregnant within one year among women now relying on reversible methods of contraception if they abandoned contraception altogether.
5. Foams, creams, gels, vaginal suppositories, and vaginal film.
6. Cervical mucus (ovulation) method supplemented by calendar in the pre-ovulatory and basal body temperature in the post-ovulatory phases.
7. With spermicidal cream or jelly.
8. Without spermicides.
9. The treatment schedule is one dose within 72 hours after unprotected intercourse, and a second dose 12 hours after the first dose. The Food and Drug Administration has declared the following brands of oral contraceptives to be safe and effective for emergency contraception: Ovral® (1 dose is 2 white pills), Alesse® (1 dose is 5 pink pills), Nordette® or Levlen® (1 dose is 4 yellow pills).
10. However, to maintain effective protection against pregnancy, another method of contraception must be used as soon as menstruation resumes, the frequency or duration of breastfeeds is reduced, bottle feeds are introduced, or the baby reaches 6 months of age.

CONTRAINDICATIONS

Progestin-only oral contraceptives (POPs) should not be used by women who currently have the following conditions:

- Known or suspected pregnancy
- Known or suspected carcinoma of the breast
- Undiagnosed abnormal genital bleeding
- Hypersensitivity to any component of this product
- Benign or malignant liver tumors
- Acute liver disease

WARNINGS

Cigarette smoking greatly increases the possibility of suffering heart attacks and strokes. Women who use oral contraceptives are strongly advised not to smoke.

Nora-BE does not contain estrogen and, therefore, this insert does not discuss the serious health risks that have been associated with the estrogen component of combined oral contraceptives. The health care provider is referred to the prescribing information of combined oral contraceptives for a discussion of those risks, including, but not limited to, an increased risk of serious cardiovascular disease in women who smoke, carcinoma of the breast and reproductive organs, hepatic neoplasia, and changes in carbohydrate and lipid metabolism. The relationship between progestin-only oral contraceptives and these risks have not been established and there are no studies definitely linking progestin-only pill (POP) use to an increased risk of heart attack or stroke.

The physician should remain alert to the earliest manifestation of symptoms of any serious disease and discontinue oral contraceptive therapy when appropriate.

1. Ectopic pregnancy. The incidence of ectopic pregnancies for progestin-only oral contraceptive users is 5 per 1000 woman-years. Up to 10% of pregnancies reported in clinical studies of progestin-only oral contraceptive users are extrauterine. Although symptoms of ectopic pregnancy should be watched for, a history of ectopic pregnancy need not be considered a contraindication to use of this contraceptive method. Health providers should be alert to the possibility of an ectopic pregnancy in women who become pregnant or complain of lower abdominal pain while on progestin-only oral contraceptives.

2. Delayed follicular atresia/Ovarian cysts. If follicular development occurs, atresia of the follicle is sometimes delayed, and the follicle may continue to grow beyond the size it would attain in a normal cycle. Generally these enlarged follicles disappear spontaneously. Often they are asymptomatic; in some cases they are associated with mild abdominal pain. Rarely they may twist or rupture, requiring surgical intervention.

3. Irregular genital bleeding. Irregular menstrual patterns are common among women using progestin-only oral contraceptives. If genital bleeding is suggestive of infection, malignancy or other abnormal conditions, such nonpharmacologic causes should be ruled out. If prolonged amenorrhea occurs, the possibility of pregnancy should be evaluated.

4. Carcinoma of the breast and reproductive organs. Some epidemiologic studies of oral contraceptive users have reported an increased relative risk of developing breast cancer, particularly at a younger age and apparently related to duration of use. These studies have predominantly involved combined oral contraceptives and there is insufficient data to determine whether the use of POPs similarly increase the risk. Women with breast cancer should not use oral contraceptives because the role of female hormone in breast cancer has not been fully determined.

Some studies suggest that oral contraceptive use has been associated with an increase in the risk of cervical intraepithelial neoplasia in some populations of women. However, there continues to be controversy about the extent to which such findings may be due to differences in sexual behavior and other factors. There is insufficient data to determine whether the use of POPs increases the risk of developing cervical intraepithelial neoplasia.

5. Hepatic neoplasia. Benign hepatic adenomas are associated with combined oral contraceptive use, although the incidence of benign tumors is rare in the United States. Rupture of benign, hepatic adenomas may cause death through intraabdominal hemorrhage.

Studies from Britain and the U.S. have shown an increased risk of developing hepatocellular carcinoma in combined oral contraceptive users. However, these cancers are rare. There is insufficient data to determine whether POPs increase the risk of developing hepatic neoplasia.

PRECAUTIONS

1. General.

Patients should be counseled that oral contraceptives do not protect against transmission of HIV (AIDS) and other sexually transmitted diseases (STDs) such as Chlamydia, genital herpes, genital warts, gonorrhea, hepatitis B, and syphilis.

2. Physical examination and follow-up.

It is considered good medical practice for sexually active women using oral contraceptives to have annual history and physical examinations. The physical examination may be deferred until after initiation of oral contraceptives if requested by the woman and judged appropriate by the clinician.

3. Carbohydrate and lipid metabolism.

Some users may experience slight deterioration in glucose tolerance, with increases in plasma insulin, but women with diabetes mellitus who use progestin-only oral contraceptives do not generally experience changes in their insulin requirements. Nonetheless, prediabetic and diabetic women in particular should be carefully monitored while taking POPs.

Lipid metabolism is occasionally affected in that HDL, HDL2, and apolipoprotein A-I and A-II may be decreased; hepatic lipase may be increased. There is no effect on total cholesterol, HDL3, LDL, or VLDL.

4. Drug interactions.

Change in contraceptive effectiveness associated with co-administration of other products:

a. Anti-infective agents and anticonvulsants. Contraceptive effectiveness may be reduced when hormonal contraceptives are co-administered with antibiotics, anticonvulsants, and other drugs that increase the metabolism of contraceptive steroids. This could result in unintended pregnancy or breakthrough bleeding. Examples include rifampin, barbiturates, phenylbutazone, phenytoin, carbamazepine, felbamate, oxcarbazepine, topiramate, and griseofulvin.

b. Anti-HIV protease inhibitors. Several of the anti-HIV protease inhibitors have been studied with co-administration of oral contraceptives; significant changes (increase and decrease) in the plasma levels of the estrogen and progestin have been noted in some cases. The safety and efficacy of OC products may be affected with the co-administration of anti-HIV protease inhibitors. Health care providers should refer to the label of the individual anti-HIV protease inhibitors for further drug-drug interaction information.

c. Herbal products. Herbal products containing St. John's Wort (hypericum perforatum) may induce hepatic enzymes (cytochrome P450) and p-glycoprotein transporter and may reduce the effectiveness of contraceptive steroids. This may also result in breakthrough bleeding.

5. Interactions with laboratory tests.

The following endocrine tests may be affected by progestin-only oral contraceptive use:

- Sex hormone-binding globulin (SHBG) concentrations may be decreased.
- Thyroxine concentrations may be decreased, due to a decrease in thyroid binding globulin (TBG).

6. Carcinogenesis.

See WARNINGS section.

7. Pregnancy.

Many studies have found no effects on fetal development associated with long-term use of contraceptive doses of oral progestins. The few studies of infant growth and development that have been conducted have not demonstrated significant adverse effects. It is nonetheless prudent to rule out suspected pregnancy before initiating any hormonal contraceptive use.

8. Nursing mothers.

Small amounts of progestin pass into the breast milk, resulting in steroid levels in infant plasma of 1-6% of the levels of maternal plasma.^6 However, isolated post-market cases of decreased milk production have been reported in POPs. Very rarely, adverse effects in the infant/child have been reported, including jaundice.

9. Fertility following discontinuation.

The limited available data indicate a rapid return of normal ovulation and fertility following discontinuation of progestin-only oral contraceptives.

10. Headache/Migraine.

If you have a headache or a worsening migraine headache with a new pattern that is recurrent, persistent, or severe, this requires discontinuation of oral contraceptives and evaluation of the cause.

11. Gastrointestinal.

Diarrhea and/or vomiting may reduce hormone absorption resulting in decreased serum concentrations.

12. Pediatric use.

Safety and efficacy of Nora-BE have been established in women of reproductive age. Safety and efficacy are expected to be the same for postpubertal adolescents under the age of 16 and for users 16 years and older. Use of this product before menarche is not indicated.

INFORMATION FOR THE PATIENT

1. See PATIENT LABELING for detailed information.

2. Counseling issues. The following points should be discussed with prospective users before prescribing progestin-only oral contraceptives:

- The necessity of taking pills at the same time every day, including throughout all bleeding episodes.
- The need to use a backup method such as condoms and spermicides for the next 48 hours whenever a progestin-only oral contraceptive is taken 3 or more hours late.
- The potential side effects of progestin-only oral contraceptives, particularly menstrual irregularities.
- The need to inform the clinician of prolonged episodes of bleeding, amenorrhea or severe abdominal pain.
- The importance of using a barrier method in addition to progestin-only oral contraceptives if a woman is at risk of contracting or transmitting STDs/HIV.

ADVERSE REACTIONS

- Menstrual irregularity is the most frequently reported side effect.
- Frequent and irregular bleeding are common, while long duration of bleeding episodes and amenorrhea are less likely.
- Headache, breast tenderness, nausea, and dizziness are increased among progestin-only oral contraceptive users in some studies.
- Androgenic side effects such as acne, hirsutism, and weight gain occur rarely.

OVERDOSAGE

There have been no reports of serious ill effects from overdosage, including ingestion by children.

DOSAGE AND ADMINISTRATION

To achieve maximum contraceptive effectiveness, Nora-BE must be taken exactly as directed. One tablet is taken every day, at the same time. Administration is continuous, with no interruption between pill packs. See PATIENT LABELING for detailed instructions.

HOW SUPPLIED

Nora-BE® (norethindrone tablets USP 0.35 mg) are packaged in cartons of six blister cards (NDC 0480-3475-16) each containing 28 tablets. Each white, round, flat-faced bevel edge tablet is debossed with TV on one side and N62 on the other side.

STORAGE

Store at controlled room temperature 20°C to 25°C (68°F to 77°F). [See USP controlled room temperature].

Manufactured for:
Teva Pharmaceuticals
Parsippany, NJ 07054

Rev. 2/2022

NRB-001

©2022 Teva Pharmaceuticals, Inc.

DETAILED INFORMATION FOR THE PATIENT

Patients should be counseled that oral contraceptives do not protect against transmission of HIV (AIDS) and other sexually transmitted diseases (STDs) such as Chlamydia, genital herpes, genital warts, gonorrhea, hepatitis B, and syphilis.

INTRODUCTION

This leaflet is about birth control pills that contain one hormone, a progestin. Please read this leaflet before you begin to take your pills. It is meant to be used along with talking with your doctor or clinic.

Progestin-only pills are often called “POPs” or “the minipill.” POPs have less progestin than the combined birth control pill (or “the pill”) which contains both an estrogen and a progestin.

HOW EFFECTIVE ARE POPS?

About 1 in 200 (0.5%) POPs users will get pregnant in the first year if they all take POPs perfectly (that is, on time, every day). About 1 in 20 (5%) “typical” POPs users (including women who are late taking pills or miss pills) gets pregnant in the first year of use. The following table will help you compare the efficacy of different methods.

IUD: 1-2%

Depo-Provera® (injectable progesterone): 0.3%

Norplant® System (levonorgestrel implants): 0.1%

Diaphragm with spermicides: 18%

Spermicides alone: 21%

Male condom alone: 12%

Female condom alone: 21%

Cervical cap:

Women who have never given birth: 18%

Women who have given birth: 36%

Periodic abstinence: 20%

No methods: 85%

HOW DO POPS WORK?

- They make the cervical mucus at the entrance to the womb (the uterus) too thick for the sperm to get through to the egg.
- They prevent ovulation (release of the egg from the ovary) in about half the time.
- They also affect other hormones, the fallopian tubes and the lining of the uterus.

YOU SHOULD NOT TAKE POPS

- If there is any chance you may be pregnant.
- If you have breast cancer.
- If you have bleeding between your periods which has not been diagnosed.
- If you are taking certain drugs for epilepsy (seizures) or for TB. (See USING POPS WITH OTHER MEDICINES below.)
- If you are hypersensitive or allergic to any component of this product.
- If you have liver tumors, either benign or cancerous.
- If you have acute liver disease.

RISKS OF TAKING POPS

WARNING: If you have sudden or severe pain in your lower abdomen or stomach area, you may have an ectopic pregnancy or an ovarian cyst. If this happens, you should contact your doctor or clinic immediately.

1. Ectopic pregnancy. An ectopic pregnancy is a pregnancy outside the womb. Because POPs protect against pregnancy, the chance of having pregnancy outside the womb is very low. If you do get pregnant while taking POPs, you have a slightly higher chance that the pregnancy will be ectopic than do users of some other birth control methods.

2. Ovarian cysts. These cysts are small sacs of fluid in the ovary. They are more common among POP users than among users of most other birth control methods. They usually disappear without treatment and rarely cause problems.

3. Cancer of the reproductive organs and breasts. Some studies in women who use combined oral contraceptives that contain both estrogen and a progestin have reported an increase in the risk of developing breast cancer, particularly at a younger age and apparently related to duration of use. There is insufficient data to determine whether the use of POPs similarly increases this risk.

Some studies have found an increase in the incidence of cancer of the cervix in women who use oral contraceptives. However, this finding may be related to factors other than the use of oral contraceptives and there is insufficient data to determine whether the use of POPs increases the risk of developing cancer of the cervix.

4. Liver tumors. In rare cases, combined oral contraceptives can cause benign but dangerous liver tumors. These benign liver tumors can rupture and cause fatal internal bleeding. In addition, a possible but not definite association has been found with combined oral contraceptives and liver cancers in studies in which a few women who developed these very rare cancers were found to have used combined oral contraceptives for long periods of time. There is insufficient data to determine whether POPs increase the risk of liver tumors.

SEXUALLY TRANSMITTED DISEASES (STDS)

WARNING: POPs do not protect against getting or giving someone HIV (AIDS) or any other STD, such as Chlamydia, gonorrhea, genital warts or herpes.

SIDE EFFECTS

1. Irregular bleeding. The most common side effect of POPs is a change in menstrual bleeding. Your periods may be either early or late, and you may have some spotting between periods. Taking pills late or missing pills can also result in some spotting or bleeding.

2. Other side effects. Less common side effects include headaches, tender breasts, nausea and dizziness. Weight gain, acne and extra hair on your face and body have been reported, but are rare.

If you are concerned about any of these side effects, check with your doctor or clinic.

USING POPS WITH OTHER MEDICINES

Before taking a POP, inform your health care provider of any other medication, including over-the-counter medicine, that you may be taking.

If you are taking medicines for seizures (epilepsy) or tuberculosis (TB), tell your doctor or clinic. These medicines can make POPs less effective:

Medicines for seizures:

- Phenytoin (Dilantin®)
- Carbamazepine (Tegretol®)
- Phenobarbital

Medicine for TB:

- Rifampin (Rifampicin)

Before you begin taking any new medicines be sure your doctor or clinic knows you are taking birth control pills that contain a progestin.

HOW TO TAKE POPS

IMPORTANT POINTS TO REMEMBER

- POPs must be taken at the same time every day, so choose a time and then take the pill at the same time every day. Every time you take a pill late, and especially if you miss a pill, you are more likely to get pregnant.
- Start the next pack the day after the last pack is finished. There is no break between packs. Always have your next pack of pills ready.
- You may have some menstrual spotting between periods. Do not stop taking your pills if this happens.
- If you vomit soon after taking a pill, use a backup method (such as condom and/or spermicide) for 48 hours.
- If you want to stop taking POPs, you can do so at any time, but, if you remain sexually active and don't wish to become pregnant, be certain to use another birth control method.
- If you are not sure about how to take POPs, ask your doctor or clinic.

STARTING POPS

- It's best to take your first POP on the first day of your menstrual period.
- If you decide to take your first POP on another day, use a backup method (such as condom and/or spermicide) every time you have sex during the next 48 hours.
- If you have had a miscarriage or an abortion, you can start POPs the next day.

IF YOU ARE LATE OR MISS TAKING YOUR POPS

- If you are more than 3 hours late or you miss one or more POPs:

1. TAKE a missed pill as soon as you remember that you missed it,
2. THEN go back to taking POPs at your regular time,
3. BUT be sure to use a backup method (such as condom and/or spermicide) every time you have sex for the next 48 hours.

- If you are not sure what to do about the pills you have missed, keep taking POPs and use a backup method until you can talk to your doctor or clinic.

IF YOU ARE BREASTFEEDING

- If you are fully breastfeeding (not giving your baby any food or formula), you may start your pills 6 weeks after delivery.
- If you are partially breastfeeding (giving your baby some food or formula), you should start taking pills by 3 weeks after delivery.

IF YOU ARE SWITCHING PILLS

- If you are switching from the combined pills to POPs, take the first POP the day after you finish the last active combined pill. Do not take any of the 7 inactive pills from the combined pill pack. You should know that many women have irregular periods after switching to POPs, but this is normal and to be expected.
- If you are switching from POPs to the combined pills, take the first active combined pill on the first day of your period, even if your POPs pack is not finished.
- If you switch to another brand of POPs, start the new brand anytime.
- If you are breastfeeding, you can switch to another method of birth control at any time, except do not switch to the combined pills until you stop breastfeeding or at least until 6 months after delivery.

PREGNANCY WHILE ON THE PILL

If you become pregnant, or think you might be, stop taking POPs and contact your physician. Even though research has shown that POPs do not cause harm to the unborn baby, it is always best not to take any drugs or medicines that you don't need when you are pregnant.

You should get a pregnancy test:

- If your period is late and you took one or more pills late or missed taking them and had sex without a backup method.
- Anytime you miss 2 periods in a row.

WILL POPS AFFECT YOUR ABILITY TO GET PREGNANT LATER?

If you want to become pregnant, simply stop taking POPs. POPs will not delay your ability to get pregnant.

BREASTFEEDING

If you are breastfeeding, POPs will not affect the quality or amount of your breast milk or the health of your nursing baby. However, isolated cases of decreased milk production have been reported. If you suspect that you are not producing enough milk for your baby, contact your doctor or clinic.

OVERDOSE

No serious problems have been reported when many pills were taken by accident, even by a small child, so there is usually no reason to treat an overdose.

OTHER QUESTIONS OR CONCERNS

WARNING: Cigarette smoking greatly increases the possibility of suffering heart attacks and strokes. Women who use oral contraceptives are strongly advised not to smoke.

Diabetic women taking POPs do not generally require changes in the amount of insulin they are taking. However, your physician may monitor you more closely under these conditions.

If you have any questions or concerns, check with your doctor or clinic. You can also ask for the more detailed “professional package labeling” written for doctors and other health care providers.

HOW TO STORE YOUR POPS

Store your POPs at room temperature 68°F to 77°F (20°C to 25°C).

Keep out of reach of children.

Manufactured for:
Teva Pharmaceuticals
Parsippany, NJ 07054

Revised 2/2022

NRBPL-001

©2022 Teva Pharmaceuticals, Inc.

PRINCIPAL DISPLAY PANEL

NDC 0480-3475-16

Nora-BE®
(Norethindrone Tablets USP)

0.35 mg

This product (like all oral contraceptives) is intended to prevent pregnancy. It does not protect against HIV infection (AIDS) and other sexually transmitted diseases.

Rx only

6 Tablet Dispensers
28 Tablets Each

Teva